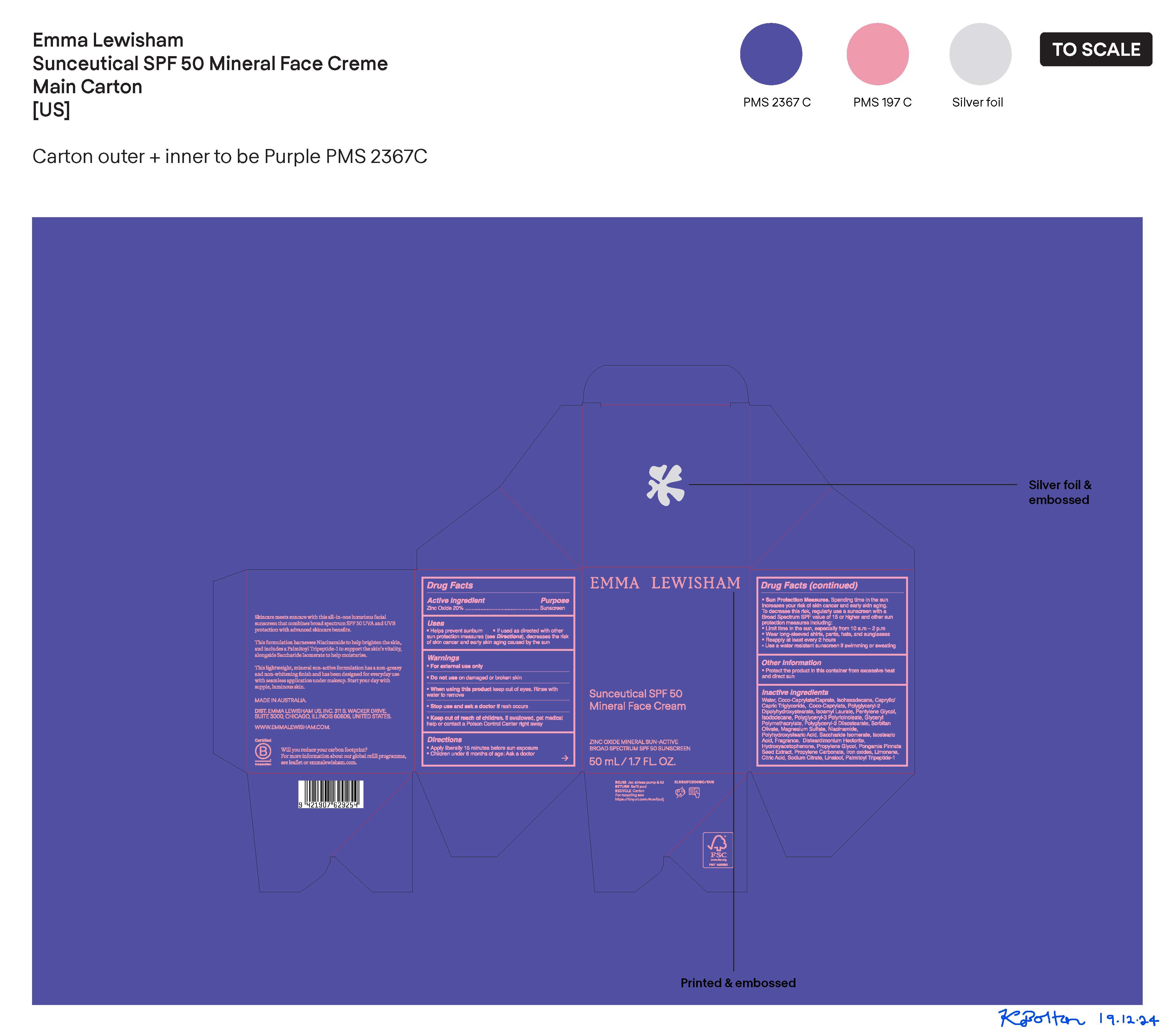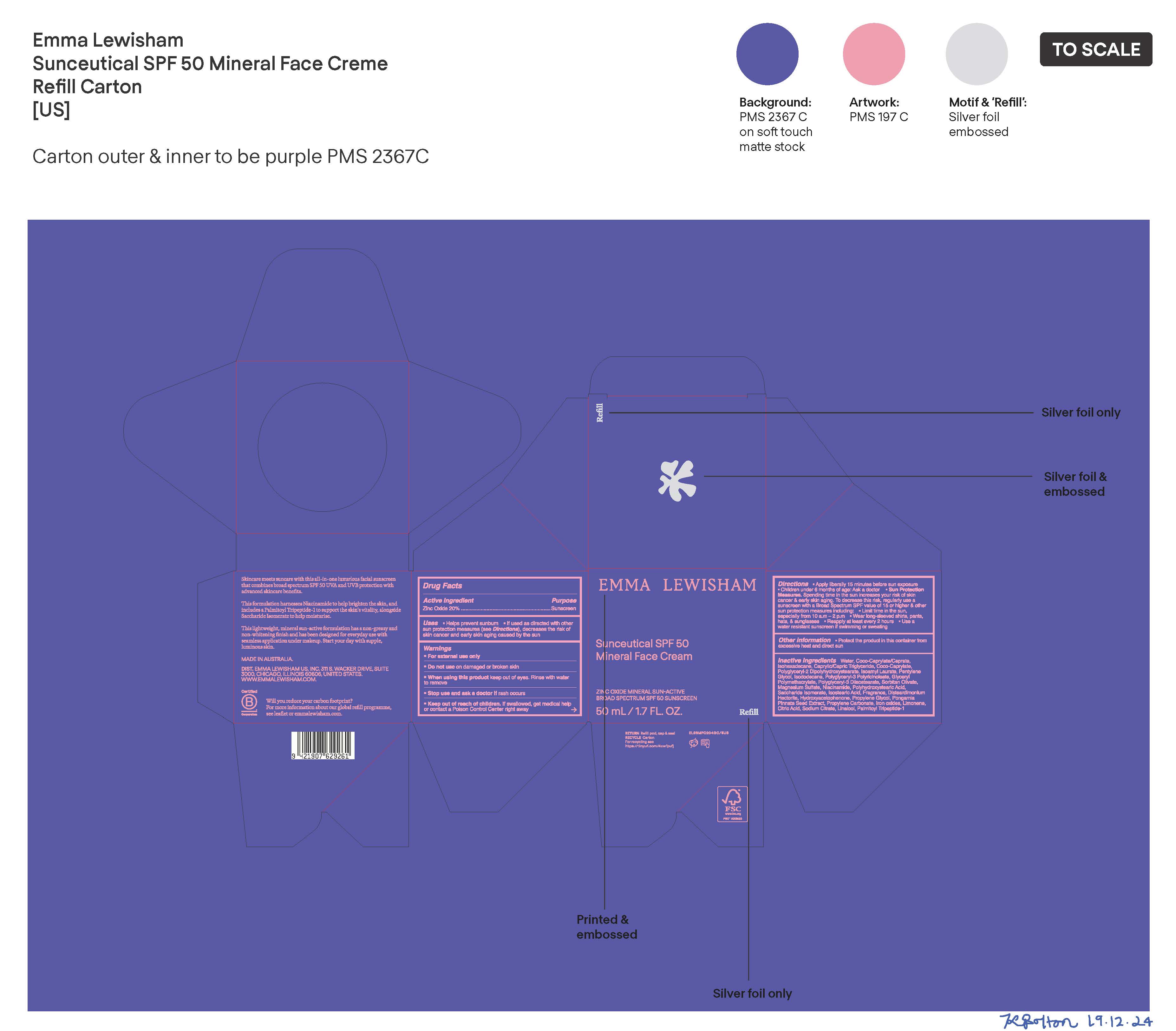 DRUG LABEL: Sunceutical SPF 50 Mineral Face Cream
NDC: 70157-369 | Form: CREAM
Manufacturer: Baxter Laboratories Pty. Ltd.
Category: otc | Type: HUMAN OTC DRUG LABEL
Date: 20250121

ACTIVE INGREDIENTS: ZINC OXIDE 20 g/100 mL
INACTIVE INGREDIENTS: WATER; HYDROXYACETOPHENONE; CAPRYLIC/CAPRIC TRIGLYCERIDE; ISOAMYL LAURATE; COCO-CAPRYLATE; PENTYLENE GLYCOL; DISTEARDIMONIUM HECTORITE; ISODODECANE; GLYCERYL POLYMETHACRYLATE (300000 MPA.S); ISOHEXADECANE; POLYGLYCERYL-2 DIPOLYHYDROXYSTEARATE; MAGNESIUM SULFATE; LINALOOL; PALMITOYL TRIPEPTIDE-1; POLYGLYCERYL-3 DIISOSTEARATE; POLYGLYCERYL-3 PENTARICINOLEATE; CITRIC ACID; SODIUM CITRATE; PROPYLENE GLYCOL; SORBITAN OLIVATE; NIACINAMIDE; ISOSTEARIC ACID; LIMONENE, (+)-; POLYHYDROXYSTEARIC ACID (2300 MW); SACCHARIDE ISOMERATE; PONGAMIA PINNATA SEED; PROPYLENE CARBONATE; COCO-CAPRYLATE/CAPRATE; IRON OXIDES

Sunceutical SPF 50 Mineral Face Cream

Active ingredient Purpose

Zinc Oxide 20%...Sunscreen

Uses

- Helps prevent sunburn
- If used as directed with other sun protection measures (see Directions), decreases the risk of skin cancer and early skin aging caused by the sun

Keep out of reach of children. If swallowed, get medical help or contact a Poison Control Center right away.

Stop use and ask a doctor if rash occurs

Warnings

- For external use only
- Do not use on damaged or broken skin
- When using this product keep out of eyes. Rinse with water to remove.

Directions

- Apply liberally 15 minutes before sun exposure
- Children under 6 months of age: Ask a doctor
- Sun Protection Measures. Spending time in the sun increases your risk of skin cancer and early skin aging. To decrease this risk, regularly use a sunscreen with a Broad Spectrum SPF value of 15 or higher and other sun protection measures including:
- Limit time in the sun, especially from 10 a.m. - 2 p.m.
- Wear long-sleeved shirts, pants, hats, and sunglasses
- Reapply at least every 2 hours
- Use a water resistant sunscreen if swimming or sweating

Other information

- Protect the product in this container from excessive heat and direct sun

Inactive ingredients

Water, Coco-Caprylate/Caprate, Isohexadecane, Caprylic/Capric Triglyceride, Coco-Caprylate, Polyglyceryl-2 Dipolyhydroxystearate, Isoamyl Laurate, Pentylene Glycol, Isododecane, Polyglyceryl-3 Polyricinoleate, Glyceryl Polymethacrylate, Polyglyceryl-3 Diisostearate, Sorbitan Olivate, Magnesium Sulfate, Niacinamide, Polyhyroxystearic Acid, Saccharide Isomerate, Isostearic Acid, Fragrance, Disteardimonium Hectorite, Hydroxyacetophenone, Propylene Glycol, Pongamia Pinnata Seed Extract, Propylene Carbonate, Iron oxides, Limonene, Citric Acid, Sodium Citrate, Linalool, Palmitoyl Tripeptide-1

PACKAGE LABEL

Emma Lewisham

Sunceutical SPF 50 Mineral Face Cream

Zinc Oxide Mineral Sun-Active

Broad Spectrum SPF 50 Sunscreen

50mL/ 1.7 FL. OZ.